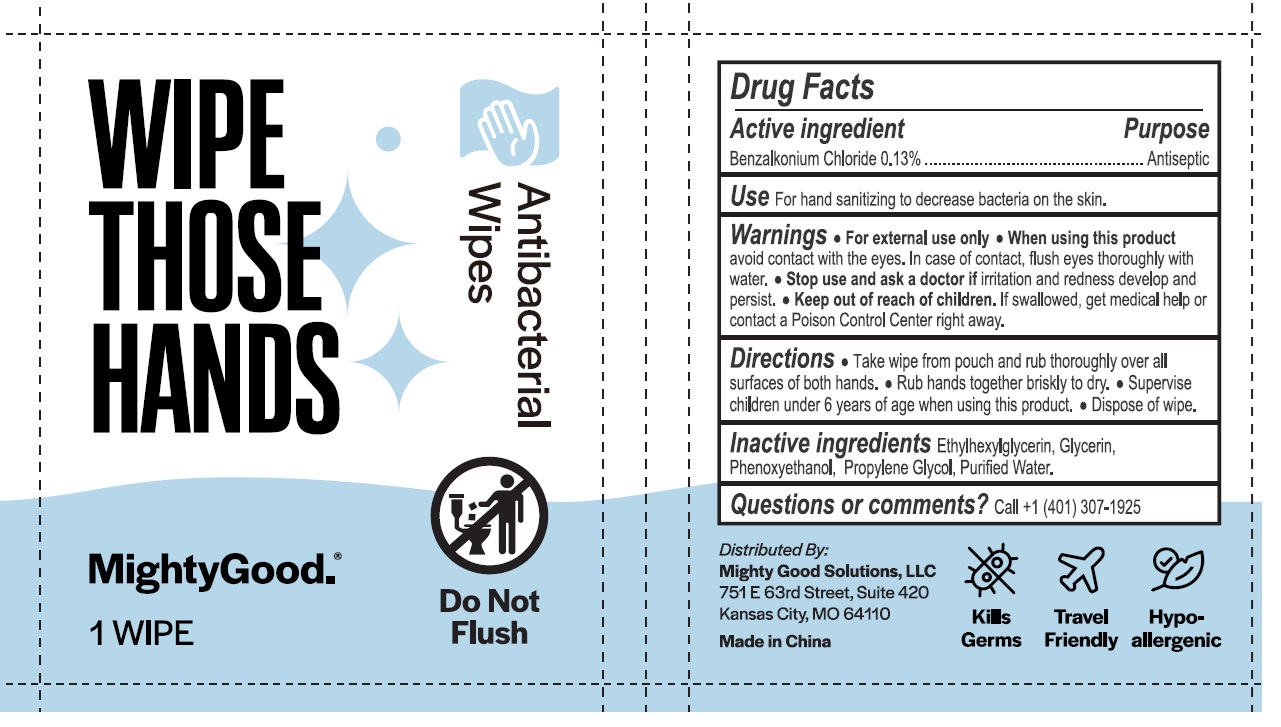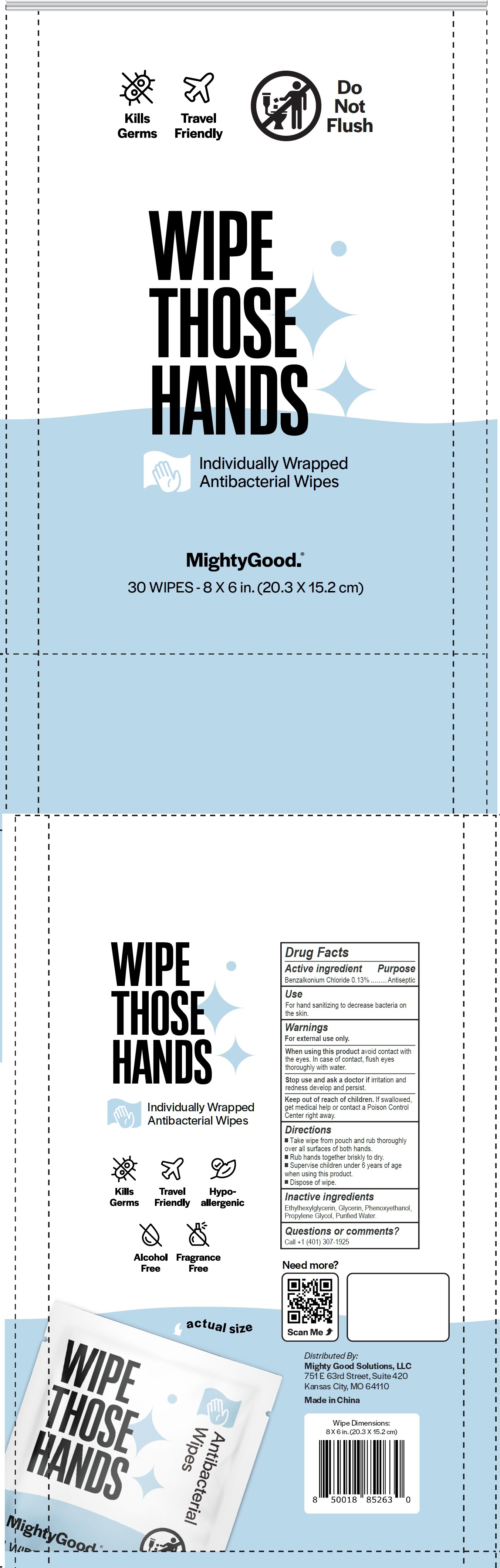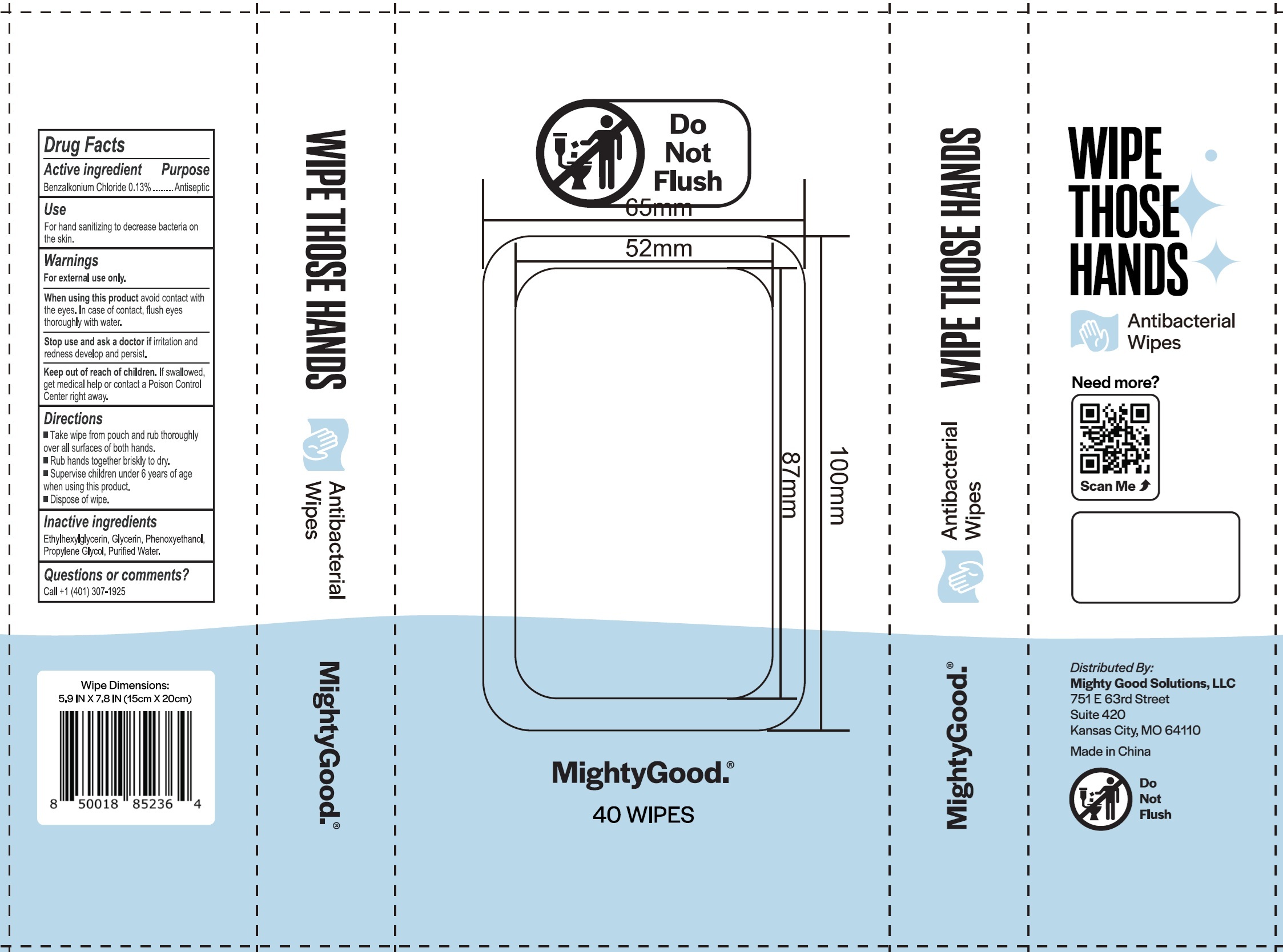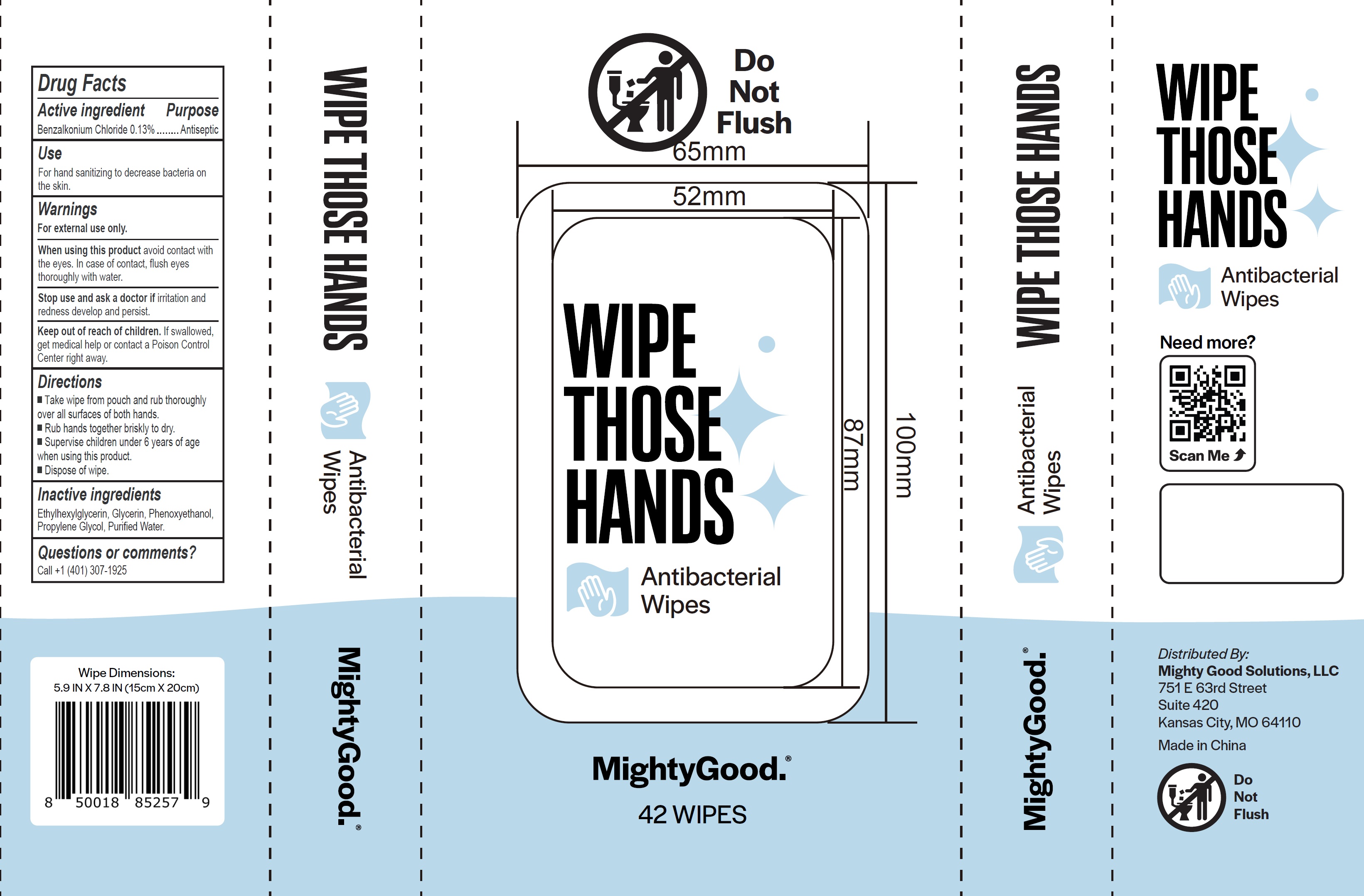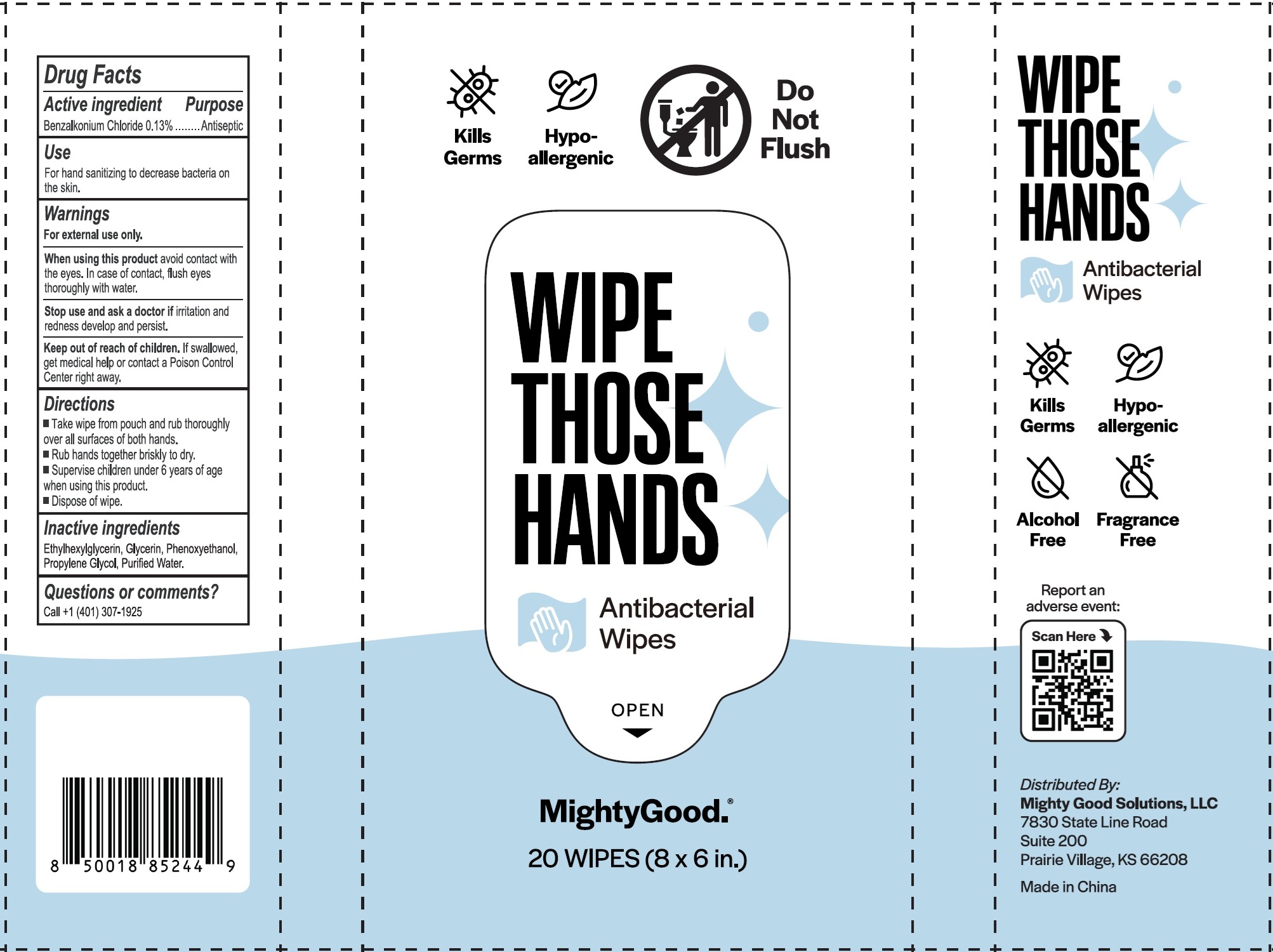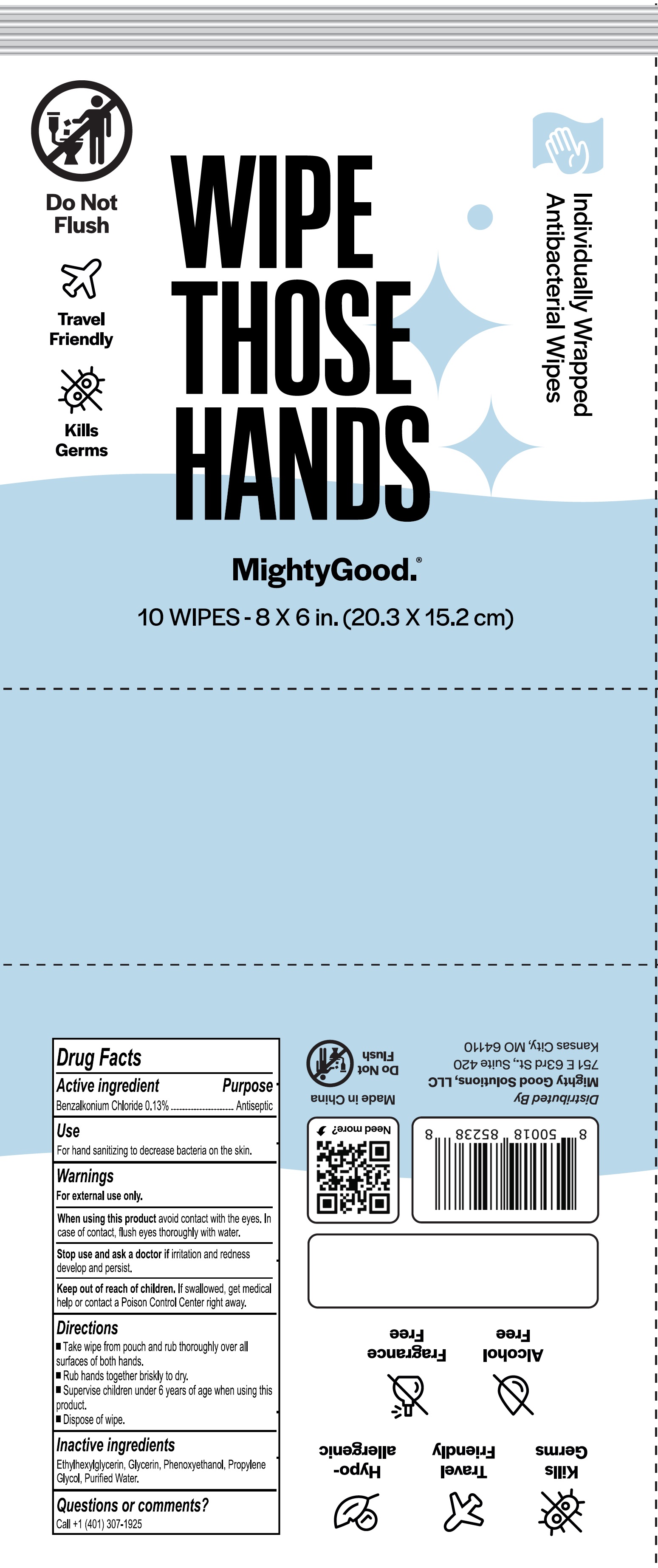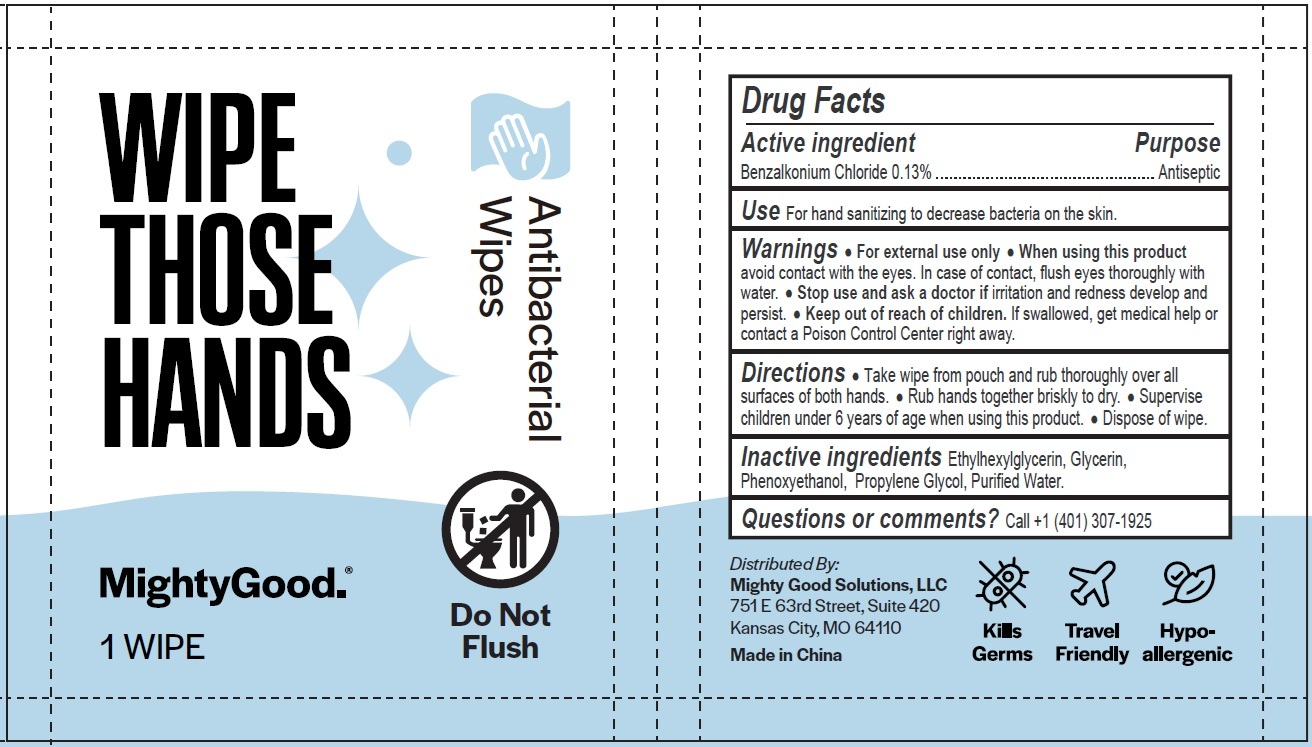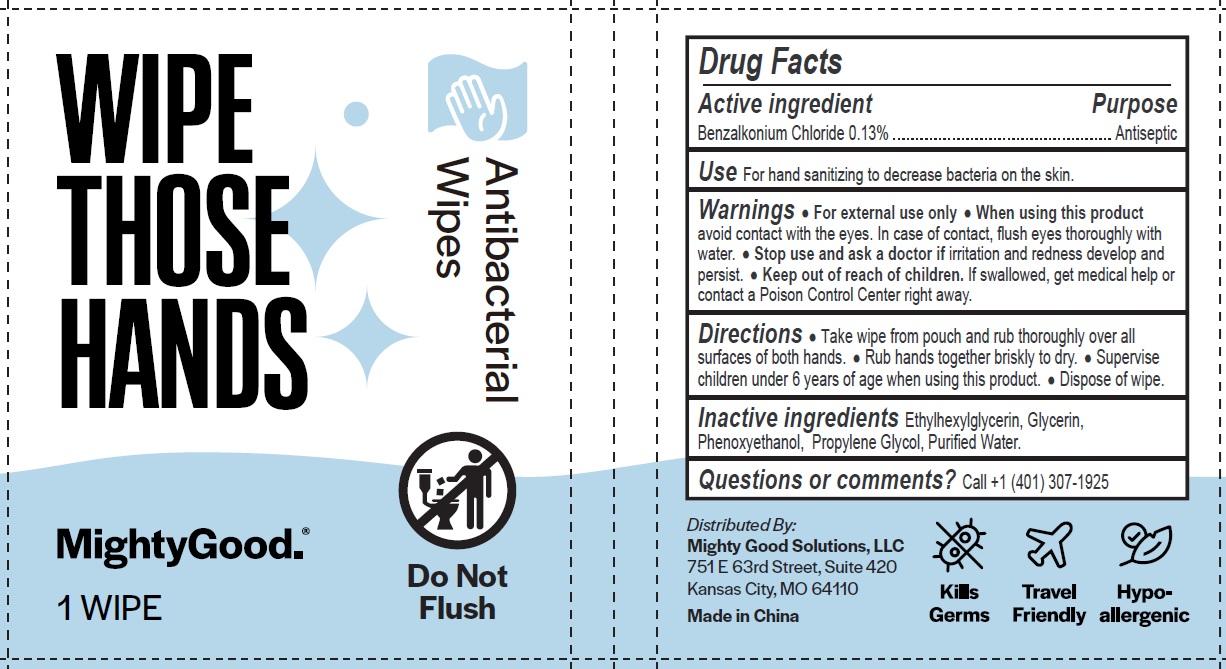 DRUG LABEL: Wipe Those Hands
NDC: 78091-251 | Form: CLOTH
Manufacturer: Mighty Good Solutions, LLC
Category: otc | Type: HUMAN OTC DRUG LABEL
Date: 20251007

ACTIVE INGREDIENTS: BENZALKONIUM CHLORIDE 1.3 mg/1 mL
INACTIVE INGREDIENTS: WATER; ETHYLHEXYLGLYCERIN; GLYCERIN; PHENOXYETHANOL; PROPYLENE GLYCOL

Wipe Those Hands

Active ingredient

Benzalkonium Chloride 0.13%

Purpose

Antiseptic

Use

For hand sanitizing to decrease bacteria on the skin.

Warnings

For external use only.

When using this product

avoid contact with the eyes. In case of contact, flush eyes thoroughly with water.

Stop use and ask a doctor if

irritation and redness develop and persist.

Keep out of reach of children.

If swallowed, get medical help or contact a Poison Control Center right away.

Directions

- Take wipe from pouch and rub thoroughly over all surfaces of both hands.
- Rub hands together briskly to dry.
- Supervise children under 6 years of age when using this product.
- Dispose of wipe.

Inactive ingredients

Ethylhexylglycerin, Glycerin, Phenoxyethanol, Propylene Glycol, Purified Water.

Questions or comments?

Call +1 (401) 307-1925